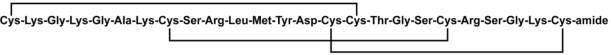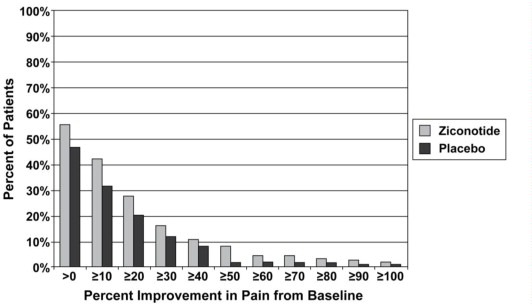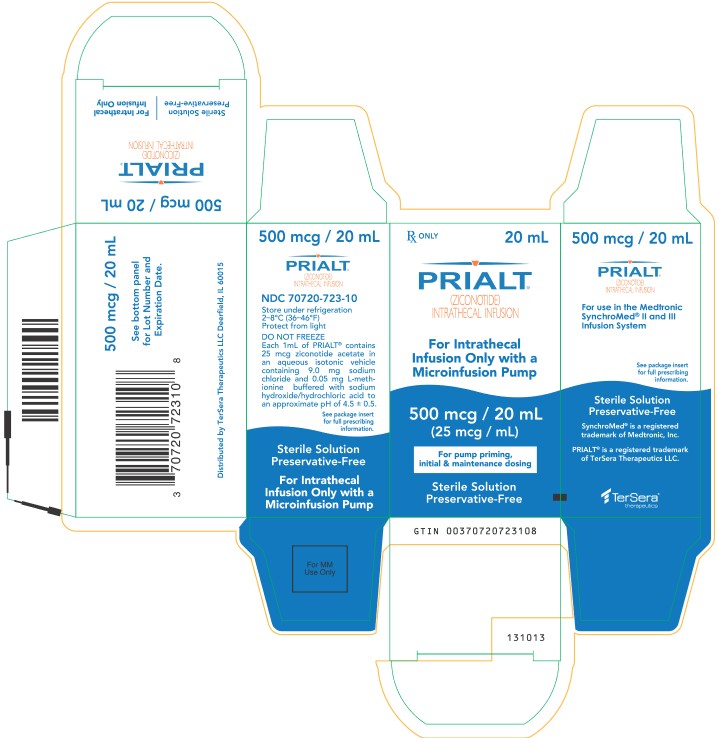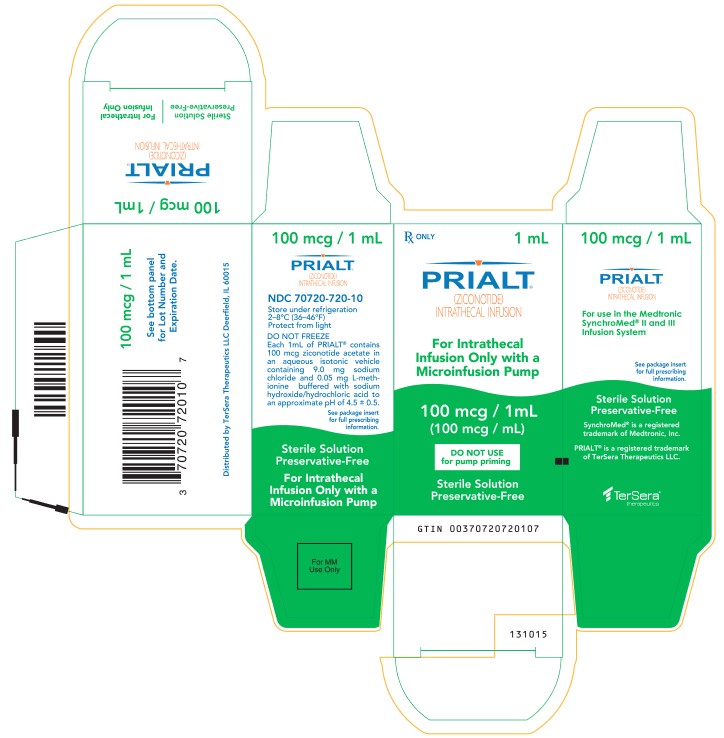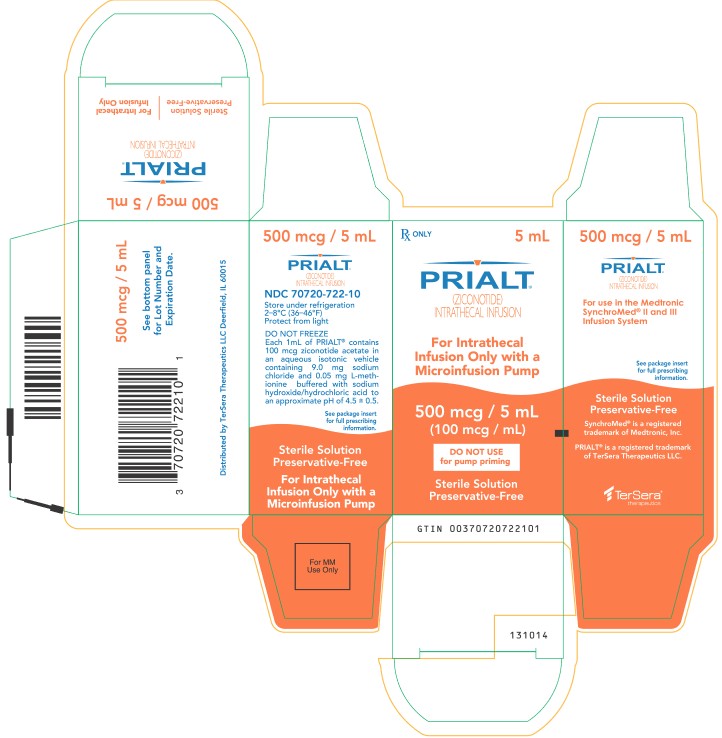 DRUG LABEL: PRIALT
NDC: 70720-723 | Form: INJECTION, SOLUTION
Manufacturer: TerSera Therapeutics LLC
Category: prescription | Type: HUMAN PRESCRIPTION DRUG LABEL
Date: 20250531

ACTIVE INGREDIENTS: ziconotide acetate 25 ug/1 mL
INACTIVE INGREDIENTS: METHIONINE; SODIUM CHLORIDE

HIGHLIGHTS OF PRESCRIBING INFORMATION

These highlights do not include all the information needed to use PRIALT safely and effectively. See full prescribing information for PRIALT.
PRIALT (ziconotide) solution, intrathecal infusion
Initial U.S. Approval: 2004

WARNING: NEUROPSYCHIATRIC ADVERSE REACTIONS

See full prescribing information for complete boxed warning

Severe psychiatric symptoms and neurological impairment may occur during treatment with PRIALT. Do not treat patients with a pre-existing history of psychosis with PRIALT

1 INDICATIONS AND USAGE

PRIALT (ziconotide) solution, intrathecal infusion is an N-type calcium channel antagonist indicated for the management of severe chronic pain in patients for whom intrathecal therapy is warranted, and who are intolerant of or refractory to other treatment, such as systemic analgesics, adjunctive therapies, or intrathecal morphine. (1)

2 DOSAGE AND ADMINISTRATION

PRIALT is a non-opioid and non-NSAID analgesic agent used for the management of severe and chronic pain. Administer PRIALT intrathecally by or under the direction of a physician experienced in the technique of intrathecal administration and who is familiar with the drug and device labeling. (2)

- PRIALT is not for intravenous administration. (2.1)
- PRIALT is delivered using a programmable implanted variable-rate microinfusion device or an external microinfusion device and catheter. (2.1)
- PRIALT 25 mcg/mL is used undiluted. The 100 mcg/mL formulation must be used diluted until an appropriate dose has been established. (2.1)
- Saline solutions containing preservatives must not be used. (2.1)
- Refrigerate but do not freeze all PRIALT solutions after preparation. Begin infusion within 24 hours. (2.1)
- Initiate PRIALT at no more than 2.4 mcg/day (0.1 mcg/hr) and titrated to patient response. Doses may be titrated upward by up to 2.4 mcg/day (0.1 mcg/hr) at intervals of no more than 2–3 times per week, up to a recommended maximum of 19.2 mcg/day (0.8 mcg/hr) by Day 21. (2)

3 DOSAGE FORMS AND STRENGTHS

Intrathecal solution (3):

- 25 mcg/mL
- 100 mcg/mL

4 CONTRAINDICATIONS

- Patients with a known hypersensitivity to ziconotide or any of its formulation components and in patients with any other concomitant treatment or medical condition that would render intrathecal administration hazardous. (4)
- Patients with a pre-existing history of psychosis with ziconotide. (4)
- Contraindications to the use of intrathecal analgesia include conditions such as the presence of infection at the microinfusion injection site, uncontrolled bleeding diathesis, and spinal canal obstruction that impairs circulation of cerebrospinal fluid (CSF). (4)

5 WARNINGS AND PRECAUTIONS

- Cognitive and neuropsychiatric adverse reactions – Cognitive impairment and severe neuropsychiatric symptoms may occur with PRIALT use. (5.1)
- Meningitis and other infections – Patients, caregivers, and healthcare providers must be aware of the signs and symptoms of meningitis, including but not limited to fever, headache, stiff neck, altered mental status (e.g., lethargy, confusion, disorientation), nausea or vomiting, and occasionally seizures. (5.2)
- Reduced level of consciousness – Patients may become unresponsive or stuporous while receiving PRIALT. (5.3)
- Elevation of serum creatine kinase – Patients taking PRIALT may experience elevations in creatine kinase. Monitor serum CK in patients undergoing treatment with PRIALT periodically. (5.4)
- Withdrawal from opiates: Patients must not be abruptly withdrawn from opiates and must be gradually tapered over a few weeks and replaced with a pharmacologically equivalent dose of oral opiates. (5.5)

6 ADVERSE REACTIONS

The most frequently reported adverse reactions (≥ 25%) in clinical trials were dizziness, nausea, confusional state, nystagmus. (6)

To report SUSPECTED ADVERSE REACTIONS, contact TerSera Therapeutics at 1-844-344-4035 or FDA at 1-800-FDA-1088 or www.fda.gov/medwatch

7 DRUG INTERACTIONS

- Combination of PRIALT with intrathecal opiates is not recommended. (7)
- Patients taking concomitant antiepileptics, neuroleptics, sedatives, or diuretics may be at higher risk of depressed levels of consciousness. (5.3)
- The use of PRIALT may be associated with an increased incidence of CNS adverse reactions such as dizziness and confusion. (7.1)

8 USE IN SPECIFIC POPULATIONS

- Geriatric Use: There is a higher incidence of confusion in elderly patients. The dose selection for an elderly patient should be cautious, starting at the low end of the dosing range. (8.5)

FULL PRESCRIBING INFORMATION

WARNING: NEUROPSYCHIATRIC ADVERSE REACTIONS

PRIALT is contraindicated in patients with a preexisting history of psychosis. Severe psychiatric symptoms and neurological impairment may occur during treatment with PRIALT. Monitor all patients frequently for evidence of cognitive impairment, hallucinations, or changes in mood or consciousness. Discontinue PRIALT therapy in the event of serious neurological or psychiatric signs or symptoms.

1 INDICATIONS AND USAGE

PRIALT (ziconotide) solution, intrathecal infusion is indicated for the management of severe chronic pain in adult patients for whom intrathecal therapy is warranted, and who are intolerant of or refractory to other treatment, such as systemic analgesics, adjunctive therapies, or intrathecal morphine.

2 DOSAGE AND ADMINISTRATION

2.1 General Information

PRIALT is intended for administration by or under the direction of a physician experienced in the technique of intrathecal administration and who is familiar with the drug and device labeling.

PRIALT is not intended for intravenous administration.

PRIALT is intended for intrathecal delivery using the Medtronic SynchroMed® II and SynchroMed® III Infusion System [see Warnings and Precautions (5.2)]. Refer to the manufacturer's manual for specific instructions and precautions for programming the microinfusion device and/or refilling the reservoir.

PRIALT may be used for therapy undiluted (25 mcg/mL in 20 mL vial) or diluted (100 mcg/mL in 1 or 5 mL vials). The 100 mcg/mL formulation may be administered undiluted once an appropriate dose has been established.

Dilute PRIALT with 0.9% Sodium Chloride Injection, USP (preservative free) using aseptic procedures to the desired concentration prior to placement in the microinfusion pump.

- Saline solutions containing preservatives are not appropriate for intrathecal drug administration and should not be used due to risk of neurotoxicity.
- Refrigerate but do not freeze all PRIALT solutions after preparation and begin infusion within 24 hours.

Inspect vials of PRIALT visually for particulate matter and discoloration prior to administration whenever solution and container permit. Discard any PRIALT solution with observed particulate matter or discoloration and any unused portion left in the vial.

2.2 Dosing

Dose Initiation

Initiate dosing with PRIALT via intrathecal device at no more than 2.4 mcg/day (0.1 mcg/hr).

Dose Titration

Titrate doses by up to 2.4 mcg/day (0.1 mcg/hr) at intervals of no more than 2 to 3 times per week based on analgesic response and adverse events. Dose increases in increments of less than 2.4 mcg/day (0.1 mcg/hr) and less frequently than 2 to 3 times per week may be used. For each dose titration, assess the dosing requirements and adjust the pump infusion flow rate as required to achieve the new dosing.

The maximum recommended dose is 19.2 mcg/day (0.8 mcg/hr).

Adjust the dose of intrathecal PRIALT according to the severity of pain, the patient's response to therapy, and the occurrence of adverse reactions.

2.3 Instructions for Use with the Medtronic SynchroMed II and SynchroMed III Infusion System

Refer to the manufacturer's manuals for specific instructions and precautions for performing a reservoir rinse, initial filling, refilling the reservoir, and programming. [see Warnings and Precautions (5.2)]

Naïve Pump Priming (i.e., first time use with PRIALT)

Use only the undiluted 25 mcg/mL formulation for naïve pump priming. Rinse the internal surfaces of the pump with 2 mL of PRIALT at 25 mcg/mL. Repeat twice for a total of three rinses.

Initial Pump Fill

Use only the undiluted 25 mcg/mL formulation for the initial pump fill. Fill the naïve pump after priming with the appropriate volume of PRIALT 25 mcg/mL. Begin dosing at a delivery rate no higher than 2.4 mcg/day (0.1 mcg/hr). In a naïve pump, PRIALT is lost due to two factors that do not occur upon subsequent refills: adsorption on internal device surfaces, such as titanium, and by dilution in the residual space of the device. Consequently, the pump reservoir should be refilled with PRIALT within 14 days of the initial fill to ensure appropriate dose administration.

Pump Refills

For subsequent pump refills, fill the pump at least every 40 days if PRIALT is used diluted. For undiluted PRIALT, fill the pump at least every 84 days. To ensure aseptic transfer of PRIALT into the device, use the Medtronic refill kit. Empty the pump contents prior to refill with PRIALT.

If the internal infusion system must be surgically replaced while the person is receiving PRIALT, rinse the replacement pump with PRIALT according to Naïve Pump Priming [see Dosage and Administration (2.4)], and replace the initial fill solution within 14 days according to Initial Pump Fill [see Dosage and Administration (2.4)].

PRIALT (ziconotide) solution, intrathecal infusion | Initial Fill Expiry | Refill Expiry
25 mcg/mL, undiluted | 14 Days | 84 Days
100 mcg/mL, undiluted | N/A | 84 Days
100 mcg/mL, diluted | N/A | 40 Days

3 DOSAGE FORMS AND STRENGTHS

PRIALT (ziconotide) solution, intrathecal infusion is supplied as a 25 mcg/mL concentration in single-use 20 mL glass vials and as a 100 mcg/mL concentration in single-use glass vials containing 1 mL or 5 mL of solution.

4 CONTRAINDICATIONS

- PRIALT is contraindicated in patients with a known hypersensitivity to ziconotide or any of its formulation components.
- PRIALT is contraindicated in patients with any other concomitant treatment or medical condition that would render intrathecal administration hazardous. Contraindications to the use of intrathecal analgesia include the presence of infection at the microinfusion injection site, uncontrolled bleeding diathesis, and spinal canal obstruction that impairs circulation of CSF.
- PRIALT is contraindicated in patients with a pre-existing history of psychosis.

5 WARNINGS AND PRECAUTIONS

5.1 Cognitive and Neuropsychiatric Adverse Reactions

Severe psychiatric symptoms and neurological impairment may occur during treatment with PRIALT. PRIALT is contraindicated in patients with a pre-existing history of psychosis. Monitor all patients frequently for evidence of cognitive impairment, hallucinations, or changes in mood or consciousness. PRIALT therapy can be interrupted or discontinued abruptly without evidence of withdrawal effects in the event of serious neurological or psychiatric signs or symptoms.

Events of acute psychiatric disturbances such as hallucinations (12%), paranoid reactions (3%), hostility (2%), delirium (2%), psychosis (1%), and manic reactions (0.4%) have been reported in patients treated with PRIALT. Patients with pretreatment psychiatric disorders may be at an increased risk. PRIALT may cause or worsen depression with the risk of suicide in susceptible patients. In placebo-controlled trials, there was a higher incidence of suicide, suicide attempts, and suicide ideations in PRIALT-treated patients than in the placebo group (0.27/patient year for PRIALT patients and 0.10/patient year for placebo patients).

Management of psychiatric complications may need to include discontinuation of PRIALT, treatment with psychotherapeutic agents and/or short-term hospitalization. Before drug is reinitiated, careful evaluation must be performed on an individual basis.

Use of PRIALT has been associated with cognitive impairment and decreased alertness/unresponsiveness. The following cognitive adverse reaction rates were reported: confusion (33%), memory impairment (22%), speech disorder (14%), aphasia (12%), thinking abnormal (8%), and amnesia (1%). Cognitive impairment may appear gradually after several weeks of treatment. Reduce the dose of PRIALT or discontinue the use of PRIALT if signs or symptoms of cognitive impairment develop, but other contributing causes must also be considered. The cognitive effects of PRIALT are generally reversible within 2 weeks after drug discontinuation. The median time to reversal of the individual cognitive effects ranged from 3 to 15 days. The elderly (≥ 65 years of age) are at higher risk for confusion. [see Use in Specific Populations (8.5)]

There may be additive effects on cognitive impairment and decreased alertness when PRIALT is used in conjunction with other CNS-depressant drugs that may necessitate dosage adjustments.

5.2 Meningitis and Other Infections

Meningitis can occur due to inadvertent contamination of the microinfusion device and other means such as CSF seeding due to hematogenous or direct spread from an infected pump pocket or catheter tract. While meningitis is rare with an internal microinfusion device and surgically-implanted catheter, the incidence increases substantially with external devices. In PRIALT clinical trials, meningitis occurred in 3% (40) of patients in the PRIALT group using either internal or external microinfusion devices and 1% (1 case) of patients in the placebo group.

The risk of meningitis was particularly high in patients with external microinfusion devices and catheters, occurring in 38 out of 41 patients (93%), 37 of whom received PRIALT and one who received placebo.

Patients, caregivers, and healthcare providers must be particularly vigilant for the signs and symptoms of meningitis, including but not limited to fever, headache, stiff neck, altered mental status (e.g., lethargy, confusion, disorientation), nausea or vomiting, and occasionally seizures. Serious infection or meningitis can occur within 24 hours of a breach in sterility such as a disconnected catheter, the most common cause of meningitis with external microinfusion devices. The patient and health care provider must be familiar with the handling of the external microinfusion device and care of the catheter skin exit site.

Strict aseptic procedures must be used during the preparation of the PRIALT solution and refilling of the microinfusion device to decrease the risk of introducing contaminants or other environmental pathogens into the reservoir. In suspected cases (especially in immuno-compromised patients) or in confirmed cases of meningitis, CSF cultures must be obtained and appropriate antibiotic therapy must be promptly instituted. Treatment of meningitis usually requires removal of the microinfusion system, catheter, and any other foreign body materials within the intrathecal space and, therefore, discontinuation of PRIALT therapy.

5.3 Reduced Level of Consciousness

Patients have become unresponsive or stuporous while receiving PRIALT. The incidence of unresponsiveness or stupor in clinical trials was 2% in PRIALT-treated patients. During these episodes, patients sometimes appear to be conscious and breathing is not depressed. If reduced levels of consciousness occur, discontinue PRIALT until the event resolves, and other etiologies (e.g., meningitis) must be considered. There is no known pharmacologic antagonist for this effect. Patients taking concomitant antiepileptics, neuroleptics, sedatives, or diuretics may be at higher risk of depressed levels of consciousness. If altered consciousness occurs, discontinue other CNS-depressant drugs as clinically appropriate.

5.4 Elevation of Serum Creatine Kinase

In clinical studies, 40% of PRIALT-treated patients had serum creatine kinase (CK) levels above the upper limit of normal (ULN), and 11% had CK levels that were greater than three times the ULN. In cases where CK was fractionated, only the muscle isoenzyme (MM) was elevated. The time to occurrence was sporadic, but the greatest incidence of CK elevation was during the first two months of treatment. One case of symptomatic myopathy with EMG findings, and two cases of acute renal failure associated with rhabdomyolysis and extreme CK elevations (17,000–27,000 IU/L) have been reported in PRIALT-treated patients.

Therefore, monitor serum CK in patients undergoing treatment with PRIALT periodically (e.g., every other week for the first month and monthly as appropriate thereafter). Evaluate patients clinically and obtain CK measurements in the setting of new neuromuscular symptoms (e.g., myalgias, myasthenia, muscle cramps, asthenia) or a reduction in physical activity. If these symptoms continue and CK levels remain elevated or continue to rise, reduce the dose or discontinue the use of PRIALT.

5.5 Withdrawal From Opiates

PRIALT is not an opiate and cannot prevent or relieve the symptoms associated with the withdrawal of opiates.

To avoid withdrawal syndrome when opiate withdrawal is necessary, do not abruptly reduce or withdraw opioid medications.

For patients being withdrawn from intrathecal opiates or intrathecal opiate infusion, gradually taper over a few weeks and replace with a pharmacologically equivalent dose of oral opiates.

5.6 Driving and Operating Machinery

Use of PRIALT has been associated with cognitive impairment and decreased alertness/unresponsiveness. Therefore, caution patients against engaging in hazardous activities that require complete mental alertness or motor coordination such as operating machinery or driving a motor vehicle.

6 ADVERSE REACTIONS

6.1 Clinical Trials Experience

Because clinical trials are conducted under widely varying conditions, adverse reaction rates observed in the clinical trials of a drug cannot be directly compared to rates in the clinical trials of another drug and may not reflect the rates in clinical practice.

A total of 1254 adult patients received PRIALT as a continuous infusion in acute and severe chronic pain trials with an exposure of 662 patient-years. The mean duration of treatment was 193 days with 173 patients (14%) treated for at least 1 year. The average final dose was 17.6 mcg/day (0.73 mcg/hr).

The most frequently reported adverse reactions (≥ 25%) in clinical trials were dizziness, nausea, confusional state and nystagmus. Slower titration of PRIALT may result in fewer serious adverse reactions and discontinuation of PRIALT for adverse reactions [see Clinical Studies (14) and Dosage and Administration (2)].

Adverse reactions during the slow titration placebo-controlled trial that occurred in 5% or greater of patients and more commonly with PRIALT than with placebo are summarized in Table 1.

Table 1. Incidence of Adverse Reactions in Slow Titration Placebo-Controlled Trial by Percent (Events That Occurred in ≥ 5% of Patients and More Commonly with PRIALT than with Placebo)
MedDRA System Organ Class MedDRA Preferred term | PRIALT N=112 | Placebo N=108
MedDRA System Organ Class MedDRA Preferred term | Percentage of Patients
Any AE | 93 | 82
Ear and Labyrinth Disorders
Vertigo | 7 | 0
Eye Disorders
Vision Blurred | 12 | 3
Gastrointestinal Disorders
Diarrhea | 18 | 15
Nausea | 40 | 29
Vomiting | 16 | 14
General Disorders and Administration Site Conditions
Asthenia | 18 | 6
Gait Abnormal | 14 | 2
Pyrexia | 5 | 3
Rigors | 7 | 5
Infections and Infestations
Sinusitis | 5 | 2
Metabolism and Nutrition Disorders
Anorexia | 6 | 2
Musculoskeletal and Connective Tissue Disorders
Muscle Spasms | 6 | 4
Pain in Limb | 5 | 2
Nervous System Disorders
Amnesia | 8 | 0
Ataxia | 14 | 1
Dizziness | 46 | 13
Dysarthria | 7 | 0
Dysgeusia | 5 | 5
Headache | 13 | 11
Memory Impairment | 7 | 1
Nystagmus | 8 | 0
Somnolence | 17 | 10
Tremor | 7 | 3
Psychiatric Disorders
Anxiety | 8 | 3
Confusional State | 15 | 5
Insomnia | 6 | 9
Renal and Urinary Disorders
Urinary Retention | 9 | 0
Skin and Subcutaneous Disorders
Pruritis | 7 | 7
Sweating Increased | 5 | 6

Other Adverse Reactions Observed During Clinical Studies of PRIALT

The following adverse reactions assessed as related to PRIALT have been reported in 2% or greater of patients participating in the clinical studies:

EYE DISORDERS: diplopia, visual disturbance

GASTROINTESTINAL DISORDERS: abdominal pain, constipation, dry mouth, nausea aggravated

GENERAL DISORDERS AND ADMINISTRATION SITE CONDITIONS: fall, fatigue, lethargy, edema peripheral

INVESTIGATIONS: blood creatine phosphokinase increased

METABOLISM AND NUTRITION DISORDERS: appetite decreased

MUSCULOSKELETAL AND CONNECTIVE TISSUE DISORDERS: muscle cramp, muscle weakness, myalgia, pain in limb

NERVOUS SYSTEM DISORDERS: aphasia, areflexia, balance impaired, burning sensation, coordination abnormal, disturbance in attention, dizziness postural, dysarthria, dysgeusia, hypoaesthesia, mental impairment, paraesthesia, sedation, speech disorder

PSYCHIATRIC DISORDERS: agitation, anxiety, cognitive disorder, confusional state, depression, depression aggravated, disorientation, hallucination, hallucination auditory, hallucination visual, insomnia, irritability, mood disorder, nervousness, paranoia

RENAL AND URINARY DISORDERS: dysuria, urinary hesitation

VASCULAR DISORDERS: hypotension, orthostatic hypotension.

The following medically important adverse reactions occurred in less than 2% of patients were assessed by the clinical investigators as related to PRIALT: acute renal failure, atrial fibrillation, cerebrovascular accident, sepsis, meningitis, psychotic disorder, suicidal ideation, respiratory distress, rhabdomyolysis, electrocardiogram abnormal, stupor, loss of consciousness, clonic convulsion and grand mal convulsion. Fatal aspiration pneumonia and suicide attempt were reported in less than 1% of patients.

6.2 Postmarketing Experience

The following adverse events have been reported during post-approval use of PRIALT. Because these events are reported voluntarily from a population of uncertain size, it is not possible to reliably estimate their frequency or establish a causal relationship to drug exposure: Hypersensitivity reactions including angioedema, serious skin reactions including bullous dermatitis, skin ulcers, skin exfoliation, and burning skin sensation.

7 DRUG INTERACTIONS

Formal PK drug-drug interaction studies have not been performed with PRIALT. As ziconotide is a peptide, it is expected to be completely degraded by endopeptidases and exopeptidases (Phase I hydrolytic enzymes) widely located throughout the body, and not by other Phase I biotransformation processes (including the cytochrome P450 system) or by Phase II conjugation reactions. Thus, intrathecal administration, low plasma ziconotide concentrations, and metabolism by ubiquitous peptidases make metabolic interactions of other drugs with ziconotide unlikely. Further, as ziconotide is not highly bound in plasma (approximately 50%) and has low plasma exposure following intrathecal administration, clinically relevant plasma protein displacement reactions involving ziconotide and co-administered medications are unlikely.

Over 90% of patients treated with intrathecal PRIALT used systemic opiates and in the slow titration study, 98% of patients received opioids.

The combination of PRIALT with intrathecal opiates has not been studied in placebo-controlled clinical trials and is not recommended.

7.1 Interaction with CNS Depressants

Almost all patients in the PRIALT clinical trials received concomitant non-intrathecal medication. Most patients received several concomitant drugs, including antidepressants (66%), anxiolytics (52%), antiepileptics (47%), neuroleptics (46%), and sedatives (34%). The use of drugs with CNS-depressant activities may be associated with an increased incidence of CNS adverse reactions such as dizziness and confusion [see Warnings and Precautions (5)].

8 USE IN SPECIFIC POPULATIONS

8.1 Pregnancy

Risk Summary

Available data from postmarketing reports are insufficient to identify a drug-associated risk of major birth defects, miscarriage, or adverse maternal or fetal outcomes. In an animal reproduction study, ziconotide did not cause embryo-fetal toxicity when administered to pregnant rats and rabbits during the period of organogenesis by continuous intravenous infusion at 400- and 940-times, respectively, the maximum recommended human dose (MRHD) of 19.2 mcg/day. In a pre- and post-natal development study, ziconotide did not affect pup development or reproductive performance when administered to rats by continuous intravenous infusion at 3800-times the MRHD (see Data).

The estimated background risk of major birth defects and miscarriage for the indicated population is unknown. All pregnancies have a background risk of birth defect, loss, or other adverse outcomes. In the U.S. general population, the estimated background risk of major birth defects and miscarriage in clinically recognized pregnancies is 2 to 4% and 15 to 20%, respectively.

Data

Animal Data

Ziconotide caused embryo-fetal mortality in rats when given as a continuous intravenous infusion during the major period of organogenesis as evidenced by significant increases in post-implantation loss because of an absence or a reduced number of live fetuses. Estimated exposure for embryo-fetal mortality in the rat was approximately 700-fold above the expected exposure resulting from the maximum recommended human daily intrathecal dose of 0.8 mcg/hr (19.2 mcg/day). Ziconotide did not result in malformations when administered to pregnant rats by continuous intravenous infusion at doses up to 30 mg/kg/day or to pregnant rabbits up to 5 mg/kg/day during the major period of organ development. Estimated exposures in the female rat and rabbit were approximately 26,000-fold and 940-fold higher than the expected exposure resulting from the maximum recommended human daily dose of 0.8 mcg/hr (19.2 mcg/day) based on plasma exposure. Maternal toxicity in the rat and rabbit, as evidenced by decreased body weight gain and food consumption, was present at all dose levels. Maternal toxicity in the rat led to reduced fetal weights and transient, delayed ossification of the pubic bones at doses ≥ 15 mg/kg/day, which is approximately 8900-fold higher than the expected exposure resulting from the maximum recommended human daily intrathecal dose of 0.8 mcg/hr (19.2 mcg/day) based on plasma exposure. The no observable adverse effect level (NOAEL) for embryo-fetal development in rats was 0.5 mg/kg/day and in rabbits was 5 mg/kg/day. Estimated NOAEL exposures in the rat and rabbit were approximately 400-fold and 940-fold higher than the expected exposure resulting from the maximum recommended human daily intrathecal dose of 0.8 mcg/hr (19.2 mcg/day) based on plasma exposure.

In a pre- and post-natal study in rats, ziconotide given as a continuous intravenous infusion did not affect pup development or reproductive performance up to a dose of 10 mg/kg/day, which is approximately 3800-fold higher than the expected exposure resulting from the maximum recommended human daily intrathecal dose of 0.8 mcg/hr (19.2 mcg/day) based on plasma exposure. Maternal toxicity, as evidenced by clinical observations, and decreases in body weight gain and food consumption were observed at all doses.

8.2 Lactation

Risk Summary

There are no data on the presence of ziconotide in either human or animal milk, the effects on the breastfed infant, or the effects on milk production. Infants exposed to PRIALT through breast milk should be monitored for sedation which may result in respiratory depression and/or feeding problems. The developmental and health benefits of breastfeeding should be weighed against the mother´s clinical need for PRIALT and any potential adverse effect on the breastfed infant from PRIALT or from the underlying maternal condition.

8.4 Pediatric Use

Safety and effectiveness in pediatric patients have not been established.

8.5 Geriatric Use

Of the total number of subjects in clinical studies of PRIALT, 22% were 65 and over, while 7% were 75 and over. In all trials, there was a higher incidence of confusion in older patients (42% for ≥ 65 year old versus 29% for < 65 year old subgroups). Other reported clinical experience has not identified differences in responses between elderly and younger patients. In general, the dose selection for an elderly patient should be cautious, usually starting at the low end of the dosing range, reflecting the greater frequency of decreased hepatic, renal or cardiac function, and of concomitant disease or other drug therapy.

10 OVERDOSAGE

The maximum recommended intrathecal PRIALT dose is 19.2 mcg/day. The maximum intrathecal dose of PRIALT in clinical trials was 912 mcg/day. In some patients who received intrathecal doses greater than the maximum recommended dose, exaggerated pharmacological effects (e.g., ataxia, nystagmus, dizziness, stupor, unresponsiveness, spinal myoclonus, confusion, sedation, hypotension, word-finding difficulties, garbled speech, nausea, and vomiting) were observed. There was no indication of respiratory depression. Overdoses may occur due to pump programming errors or incorrect drug concentration preparations. In these cases, patients were observed and ziconotide was either temporarily discontinued or permanently withdrawn. Most patients recovered within 24 hours after withdrawal of drug. In the event of an overdose, elimination of ziconotide from CSF would be expected to remain constant (CSF t½=4.6 hours). Therefore, within 24 hours of stopping therapy, the ziconotide CSF concentration should be less than 5% of peak levels.

There is no known antidote to ziconotide. General medical supportive measures should be administered to patients who receive an overdose until the exaggerated pharmacological effects of the drug have resolved. Treatment for an overdose is hospitalization, when needed, and symptom-related supportive care. Ziconotide does not bind to opiate receptors and its pharmacological effects are not blocked by opioid antagonists.

In the event of an inadvertent intravenous or epidural administration, adverse reactions could include severe hypotension, which can be treated with a recumbent posture and blood pressure support as required. The half-life of PRIALT in serum is 1.3 hours.

11 DESCRIPTION

PRIALT contains ziconotide, a synthetic equivalent of a naturally occurring conopeptide found in the piscivorous marine snail, Conus magus. Ziconotide is a 25 amino acid, polybasic peptide containing three disulfide bridges with a molecular weight of 2639 daltons and a molecular formula of C102H172N36O32S7. The amino acid sequence and disulfide bridging pattern are given below:

Ziconotide is a hydrophilic molecule that is freely soluble in water and is practically insoluble in methyl t-butyl ether.

PRIALT is formulated as a sterile, preservative-free, isotonic solution for intrathecal administration using an appropriate microinfusion device [see Dosage and Administration (2)]. Each 1 or 5 mL vial of PRIALT (100 mcg/mL) respectively contains 100 or 500 mcg of ziconotide acetate, and the 20 mL vial of PRIALT (25 mcg/mL) contains 500 mcg of ziconotide acetate, with L-methionine and sodium chloride as excipients at pH 4.0–5.0. Each vial is intended for single use only, either undiluted or after dilution to the appropriate concentration with 0.9% Sodium Chloride Injection, USP (preservative free).

12 CLINICAL PHARMACOLOGY

12.1 Mechanism of Action

Ziconotide binds to N-type calcium channels located on the primary nociceptive (A-δ and C) afferent nerves in the superficial layers (Rexed laminae I and II) of the dorsal horn in the spinal cord. Although the mechanism of action of ziconotide has not been established in humans, results in animals suggest that its binding blocks N-type calcium channels, which leads to a blockade of excitatory neurotransmitter release from the primary afferent nerve terminals and antinociception.

12.2 Pharmacodynamics

Interaction with Opioids

Ziconotide does not bind to opioid receptors and its pharmacological effects are not blocked by opioid antagonists. In animal models, intrathecal ziconotide potentiated opioid-induced reduction in gastrointestinal (GI) motility, but did not potentiate morphine-induced respiratory depression. In rats receiving ziconotide, additive analgesic effects were observed with concurrent administration of morphine, baclofen, or clonidine. Concurrent administration of intrathecal ziconotide and morphine did not prevent the development of morphine tolerance in rats.

12.3 Pharmacokinetics

The cerebrospinal fluid (CSF) pharmacokinetics (PK) of ziconotide have been studied after one-hour intrathecal infusions of 1 to 10 mcg of PRIALT to patients with chronic pain. The plasma PK following intravenous infusion (0.3 to 10 mcg/kg/day) have also been studied. Both intrathecal and intravenous data are shown below (Table 2).

Table 2. PRIALT PK Parameters (Mean ± SD)
Route | Fluid | N | CL (mL/min) | Vd (mL) | T 1/2elim (hr)
Intrathecal | CSF | 23 | 0.38 ± 0.56 | 155 ± 263 | 4.6 ± 0.9
Intravenous | Plasma | 21 | 270 ± 44 | 30,460 ± 6366 | 1.3 ± 0.3

Following one-hour intrathecal administration of 1 to 10 mcg of PRIALT, both total exposure (AUC; range: 83.6 to 608 ng•h/mL) and peak exposure (Cmax; range: 16.4 to 132 ng/mL) values in the CSF were variable and dose-dependent, but appeared approximately dose-proportional. During 5 or 6 days of continuous intrathecal infusions of PRIALT at infusion rates ranging from 0.1 to 7.0 mcg/hr in patients with chronic pain, plasma ziconotide levels could not be quantified in 56% of patients using an assay with a lower limit of detection of approximately 0.04 ng/mL. Predictably, patients requiring higher intrathecal infusion dose rates were more likely to have quantifiable ziconotide levels in plasma. Plasma ziconotide levels, when detectable, remain constant after many months of intrathecal PRIALT infusion in patients followed for up to 9 months.

Distribution

Ziconotide is about 50% bound to human plasma proteins. The mean CSF volume of distribution (Vd) of ziconotide following intrathecal administration approximates the estimated total CSF volume (140 mL).

Elimination

Metabolism

Ziconotide is cleaved by endopeptidases and exopeptidases at multiple sites on the peptide. Following passage from the CSF into the systemic circulation during continuous intrathecal administration, ziconotide is expected to be susceptible to proteolytic cleavage by various ubiquitous peptidases/proteases present in most organs (e.g., kidney, liver, lung, muscle, etc.), and thus readily degraded to peptide fragments and their individual constituent free amino acids. Human and animal CSF and blood exhibit minimal hydrolytic activity toward ziconotide in vitro. The biological activity of the various expected proteolytic degradation products of ziconotide has not been assessed.

Excretion

Minimal amounts of ziconotide (< 1%) were recovered in human urine following intravenous infusion. The terminal half-life of ziconotide in CSF after an intrathecal administration was around 4.6 hours (range 2.9 to 6.5 hours). Mean CSF clearance (CL) of ziconotide approximates adult human CSF turnover rate (0.3 to 0.4 mL/min).

Specific Populations

No formal studies were conducted to assess the effect of demographic factors (age, race, gender, and weight), renal or hepatic dysfunction, or to assess the effect of concomitant drugs on the pharmacokinetics of ziconotide due to the low systemic exposure of ziconotide following intrathecal administration.

13 NONCLINICAL TOXICOLOGY

13.1 Carcinogenesis, Mutagenesis, Impairment of Fertility

Carcinogenesis

No carcinogenicity studies have been conducted in animals.

Mutagenesis

Ziconotide was negative in the in vitro bacterial reverse mutation assay, in vitro mouse lymphoma assay, in vivo mouse micronucleus assay, and in the in vitro Syrian hamster embryo (SHE) cell transformation assay.

Impairment of Fertility

Ziconotide did not affect male fertility in rats when administered as a continuous intravenous infusion at a dose of up to 10 mg/kg/day when administered for approximately 8 weeks, including a 28-day pre-mating period, or female fertility at a dose of 3 mg/kg/day when administered for approximately 6 weeks, including a 14-day pre-mating period. Estimated exposures for the male and female rats were approximately 6500-fold and 1700-fold higher, respectively, than the expected exposure resulting from the maximum recommended human daily intrathecal dose of 0.8 mcg/hr (19.2 mcg/day) based on plasma exposure.

Female fertility in rats was significantly affected following continuous intravenous infusion at a dose of 10 mg/kg/day. Significant reductions in corpora lutea, implantation sites, and number of live fetuses were observed.

14 CLINICAL STUDIES

The efficacy of intrathecal PRIALT in the management of severe chronic pain was studied in three double-blind, placebo-controlled, multicenter studies in a total of 457 patients (268 PRIALT, 189 placebo) using two different titration schedules. The slow titration schedule tested dose increases 2 to 3 times per week with a maximum dose of 19.2 mcg/day (0.8 mcg/hr) at 21 days. The fast titration schedule used daily increases up to a maximum dose of 57.6 mcg/day (2.4 mcg/hr) in 5 to 6 days but resulted in less tolerability and substantially more frequent adverse events.

A randomized, double-blind, placebo-controlled study of PRIALT was conducted in adult patients with severe chronic pain not adequately controlled with intrathecally delivered analgesics including morphine, bupivacaine and/or clonidine; or who were intolerant to analgesics and/or systemic analgesics using the 21-day slow titration schedule. All prior intrathecal medications were discontinued over a one to three week period, and patients were maintained on a stable regimen of non-intrathecal analgesics, including opiates, for at least 7 days prior to randomization. Dosing with PRIALT was started at 2.4 mcg/day (0.1 mcg/hr) and the dose was increased by 2.4 mcg/day (0.1 mcg/hr) two to three times/week (minimum titration interval 24 hours) to a maximum dose of 19.2 mcg/day (0.8 mcg/hr) as needed for management of pain. The final mean dose at the end of the trial at 21 days was 6.9 mcg/day (0.29 mcg/hr).

Using a 100 mm Visual Analog Scale of Pain Intensity (VASPI) where 100 mm represented the worst possible pain, mean baseline pain scores were 81 in both the PRIALT and placebo groups. The primary efficacy variable was the mean percent change in the VASPI score from baseline to day 21. In the intent-to-treat efficacy analysis, there was a statistically significant difference between groups in the mean percent change in VASPI score from baseline with the PRIALT group having a 12% mean improvement at Week 3 compared to a 5% mean improvement in the placebo group. The 95% confidence interval for the treatment difference (PRIALT–placebo) was 0.4%, 13%.

The effect of intrathecal PRIALT on pain was variable over the time period of treatment for some patients. Patients exhibited various degrees of improvement in pain after three weeks of treatment compared with baseline pain assessment. Figure 1 depicts the fraction of patients by their degree of improvement. The figure is cumulative, so that patients whose change from baseline is, for example, 30%, are also included at every level of improvement below 30%. Patients who did not have a VASPI score recorded at Week 3 (Study days 17–23, inclusive) were assigned 0% improvement. The improvement in the proportion of “responders,” defined as having a ≥ 30% improvement from baseline in VASPI, was 16% in the PRIALT group compared to 12% in the placebo group, for a net difference of 4%. The use of non-intrathecal opioids decreased by 24% in the PRIALT group and by 17% in the placebo group.

Figure 1: Patients Achieving Various Levels of Pain Relief from Baseline to Week 3

14.1 Laboratory Tests

Monitor serum CK in patients undergoing treatment with PRIALT periodically (e.g., every other week for the first month and monthly as appropriate thereafter). Evaluate patients clinically and obtain CK measurements in the setting of new neuromuscular symptoms (e.g., myalgias, myasthenia, muscle cramps, asthenia) or a reduction in physical activity. If these symptoms continue and CK levels remain elevated or continue to rise, reduce the dose or discontinue the use of PRIALT.

16 HOW SUPPLIED/STORAGE AND HANDLING

16.1 How Supplied

PRIALT is supplied as a 25 mcg/mL solution in a single-use 20 mL glass vial and as a 100 mcg/mL solution in single-use glass vials containing 1 mL or 5 mL of solution. One vial is packaged per carton.

Presentation (NDC)

25 mcg/mL: 20 mL vial (70720-723-10). Only the undiluted 25 mcg/mL formulation should be used for PRIALT naïve pump priming.

100 mcg/mL: 1 mL vial (70720-720-10)
5 mL vial (70720-722-10)

16.2 Storage

- Refrigerate PRIALT during transit.
- Store PRIALT at 2°C to 8°C (36°F to 46°F).
- PRIALT, once diluted aseptically with saline, may be stored at 2°C to 8°C for 24 hours.
- Do NOT freeze PRIALT.
- Protect from light.

17 PATIENT COUNSELING INFORMATION

- Advise patients that psychiatric symptoms (paranoia, hostility, mania, depressive, suicidal) and cognitive symptoms (confusion, memory problems, speech disorder) may occur during treatment with PRIALT.
- Caution patients against engaging in hazardous activity requiring complete mental alertness or motor coordination such as operating machinery or driving a motor vehicle during treatment with PRIALT.
- Caution patients about possible combined effects with other CNS-depressant drugs. Dosage adjustments may be necessary when PRIALT is administered with such agents because of the potentially additive effects.
- Advise patients to contact a physician if the patient experiences new or worsening muscle pain, soreness, weakness with or without darkened urine.
- Instruct patients and their caregivers to contact a physician immediately if the patient has any of the following
  - A change in mental status (e.g., lethargy, confusion, disorientation, decreased alertness)
  - A change in mood, perception (hallucinations, including unusual tactile sensations in the oral cavity)
  - Symptoms of depression or suicidal ideation
  - Nausea, vomiting, seizures, fever, headache, and/or stiff neck, as these may be symptoms of developing meningitis
  - Decreased level of consciousness, unresponsiveness or stupor
  - New muscular symptoms (e.g., muscle cramps, myalgias)
  - Withdrawal symptoms (e.g., nausea, insomnia, flu-like symptoms) as a result of abruptly discontinuing opioid therapy
  - Development of serious skin reaction (e.g., bullous dermatitis, skin ulcers, skin exfoliation)
- Lactation: Advise mothers who have been administered PRIALT to monitor neonates for signs of sedation which may result in respiratory depression and/or feeding problems [see Use in Specific Populations (8.2)]

For use only in the Medtronic SynchroMed® II and SynchroMed® III Infusion System.

Distributed by:
TerSera Therapeutics, LLC
Deerfield, IL 60015
© 2023 TerSera Therapeutics
PRIALT® is a registered trademark of TerSera Therapeutics, LLC.
SynchroMed® is a registered trademark of Medtronic, Inc.
U.S. Patent Nos. 5,364,842; 5,795,864; and 5,891,849

PACKAGE LABEL

PRINCIPAL DISPLAY PANEL - 20 mL Carton

NDC 70720-723-10

Principal Display Panel

Rx ONLY 20 mL

PRIALT®
(ZICONOTIDE)
INTRATHECAL INFUSION

For Intrathecal
Infusion Only with a
Microinfusion Pump

500 mcg / 20 mL
(25 mcg / mL)

For pump priming,
initial & maintenance dosing

Sterile Solution
Preservative-Free

Left Side Panel

500 mcg / 20 mL

PRIALT®
(ZICONOTIDE)
INTRATHECAL INFUSION

NDC 70720-723-10

Store under refrigeration
2–8°C (36–46°F)
Protect from light

DO NOT FREEZE

Each 1mL of PRIALT® contains
25 mcg ziconotide acetate in
an aqueous isotonic vehicle
containing 9.0 mg sodium
chloride and 0.05 mg L-meth-
ionine buffered with sodium
hydroxide/hydrochloric acid to
an approximate pH of 4.5 ± 0.5.

See package insert
for full prescribing
information.

Sterile Solution
Preservative-Free

For Intrathecal
Infusion Only with a
Microinfusion Pump

Right Side Panel

500 mcg / 20 mL

PRIALT®
(ZICONOTIDE)
INTRATHECAL INFUSION

For use in the Medtronic
SynchroMed® II and III
Infusion System

See package insert
for full prescribing
information.

Sterile Solution
Preservative-Free

SynchroMed® is a registered
trademark of Medtronic, Inc.

PRIALT® is a registered trademark
of TerSera Therapeutics LLC.

TerSera therapeutics

Back Panel

500 mcg / 20 mL

See bottom panel
for Lot Number and
Expiration Date.

Distributed by TerSera Therapeutics LLC Deerfield, IL 60015

PACKAGE LABEL

PRINCIPAL DISPLAY PANEL - 1 mL Carton

NDC 70720-720-10

Principal Display Panel

Rx ONLY 1 mL

PRIALT®
(ZICONOTIDE)
INTRATHECAL
INFUSION

For Intrathecal
Infusion Only with a
Microinfusion Pump

100 mcg / 1 mL
(100 mcg / mL)

DO NOT USE
for pump priming

Sterile Solution
Preservative-Free

PACKAGE LABEL

PRINCIPAL DISPLAY PANEL - 5 mL Carton

NDC 70720-722-10

Principal Display Panel

Rx ONLY 5 mL

PRIALT®
(ZICONOTIDE)
INTRATHECAL
INFUSION

For Intrathecal
Infusion Only with a
Microinfusion Pump

500 mcg / 5 mL
(100 mcg / mL)

DO NOT USE
for pump priming

Sterile Solution
Preservative-Free